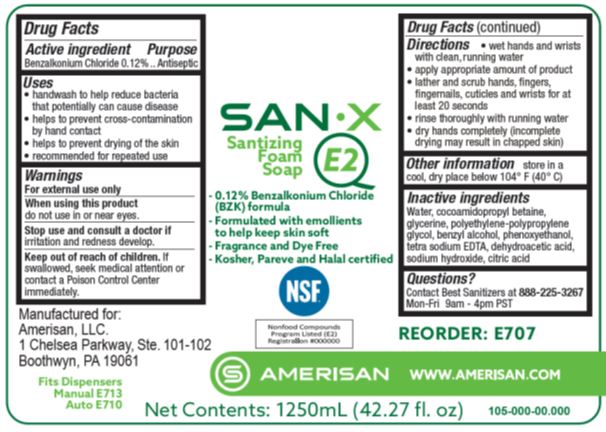 DRUG LABEL: SAN X E2
NDC: 69884-706 | Form: LIQUID
Manufacturer: Amerisan, LLC
Category: otc | Type: HUMAN OTC DRUG LABEL
Date: 20241216

ACTIVE INGREDIENTS: BENZALKONIUM CHLORIDE 0.12 g/100 mL
INACTIVE INGREDIENTS: COCAMIDOPROPYL BETAINE; GLYCERIN; BENZYL ALCOHOL; POLYETHYLENE GLYCOL 800; SODIUM HYDROXIDE; WATER; EDETATE SODIUM; DEHYDROACETIC ACID; CITRIC ACID MONOHYDRATE; PHENOXYETHANOL

SAN X E2 69884-706

Active ingredient

Benzalkonium Chloride 0.12%

Purpose

Antiseptic

Uses

- handwash to help reduce bacteria that potentially can cause disease
- helps to prevent cross-contamination by hand contact
- helps to prevent drying of the skin
- recommended for repeated use

Warnings

For external use only

WHEN USING

When using this productdo not use in or near eyes.

Stop use and consult a doctor ifirritation and redness develop.

Keep out of reach of children.

If swallowed, seek medical attention or contact a Poison Control Center immediately.

Directions

- wet hands and wrists with clean, running water
- apply appropriate amount of product
- lather and scrub hands, fingers, fingernails, cuticles and wrists for at least 20 seconds
- rinse thoroughly with running water
- dry hands completely (incomplete drying may result in chapped skin)

Other information

store in a cool, dry place below 104 F (40 C)

Inactive ingredients

Water, cocamidopropyl betaine, glycerine, polyethylene-polypropylene glycol, benzyl alcohol, phenoxyethanol, tetra sodium EDTA, dehydroacetic acid, sodium hydroxide, citric acid

Questions?

Contact Best Sanitizers at 888-225-3267Mon-Fri 9am - 4pm PST

PACKAGE LABEL

SAN X

E2

Sanitizing

Foam

Soap

- 0.12% Benzalkonium Chloride

(BZK) formula

- Formulated with emollients

to help keep skin soft

- Fragrance and Dye Free
- Kosher, Pareve and Halal certified

NSF

Nonfood Compounds

Program Listed (E2)

Registration #

AMERISAN

Net Contents: 1250 mL (42.27 fl. oz)